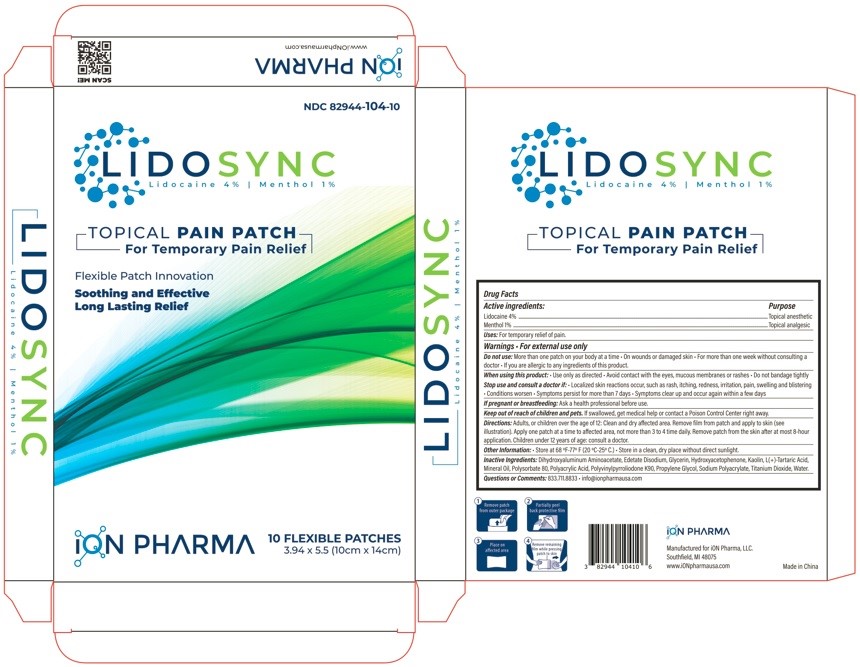 DRUG LABEL: LIDOSYNC
NDC: 82944-104 | Form: PATCH
Manufacturer: Ion Pharma, LLC
Category: otc | Type: HUMAN OTC DRUG LABEL
Date: 20260114

ACTIVE INGREDIENTS: LIDOCAINE 4 g/1 1; MENTHOL 1 g/1 1
INACTIVE INGREDIENTS: DIHYDROXYALUMINUM AMINOACETATE; DIHYDROXYALUMINUM AMINOACETATE ANHYDROUS; EDETATE DISODIUM; GLYCERIN; HYDROXYACETOPHENONE; KAOLIN; TARTARIC ACID; MINERAL OIL; POLYSORBATE 80; POLYACRYLIC ACID (250000 MW); POVIDONE K90; PROPYLENE GLYCOL; SODIUM POLYACRYLATE (2500000 MW); TITANIUM DIOXIDE; WATER

LIDOSYNC
Lidocaine 4% Menthol 1%
TOPICAL PAIN PATCH
For Temporary Pain Relief

Drug Facts

Active ingredients:
Lidocaine 4% Menthol 1%
Purpose
Topical anesthetic - Topical analgesic
INDICATIONS & USAGE
Uses: For temporary relief of pain.
Warnings
For external use only
DO NOT USE
Do not use: More than one patch on your body at a time - On wounds or damaged skin - For more than one week without consulting a doctor - If you are allergic to any ingredients of this product.
WHEN USING
When using this product: Use only as directed - Avoid contact with the eyes, mucous membranes or rashes - Do not bandage tightly
STOP USE
Stop use and consult a doctor if: Localized skin reactions occur, such as rash, itching, redness, irritation, pain, swelling and blistering - Conditions worsen - Symptoms persist for more than 7 ...
PREGNANCY OR BREAST FEEDING
If pregnant or breastfeeding: Ask a health professional before use.
KEEP OUT OF REACH OF CHILDREN
Keep out of reach of children and pets. If swallowed, get medical help or contact a Poison Control Center right away.
DOSAGE & ADMINISTRATION
Directions: Adults, or children over the age of 12: Clean and dry affected area. Remove film from patch and apply to skin (see illustration). Apply one patch at a time to affected area, not more ...
Other Information:
Store at 68 °F-77° F (20 °C-25° C.) Store in a clean, dry place without direct sunlight.
Inactive Ingredients:
Dihydroxyaluminum Aminoacetate, Edetate Disodium, Glycerin, Hydroxyacetophenone, Kaolin, L(+)-Tartaric Acid, Mineral Oil, Polysorbate 80, Polyacrylic Acid, Polyvinylpyrroliodone K90, Propylene ...
QUESTIONS
Questions or Comments: 833.711.8833 - info@ionpharmausa.com
PRINCIPAL DISPLAY PANEL
NDC 82944-104-10 - LIDOSYNC - Lidocaine 4% Menthol 1% TOPICAL PAIN PATCH - For Temporary Pain Relief - Flexible Patch Innovation - Soothing and Effective - Long Lasting Relief - 10 FLEXIBLE ...
INGREDIENTS AND APPEARANCE
Product Information

Active ingredients:

Lidocaine 4%

Menthol 1%

Purpose

Topical anesthetic

Topical analgesic

INDICATIONS AND USAGE

Uses:For temporary relief of pain.

Warnings

- For external use only

Do not use:

- More than one patch on your body at a time
- On wounds or damaged skin
- For more than one week without consulting a doctor
- If you are allergic to any ingredients of this product.

When using this product:

- Use only as directed
- Avoid contact with the eyes, mucous membranes or rashes
- Do not bandage tightly

Stop use and consult a doctor if:

- Localized skin reactions occur, such as rash, itching, redness, irritation, pain, swelling and blistering
- Conditions worsen
- Symptoms persist for more than 7 days
- Symptoms clear up and occur again within a few days

PREGNANCY OR BREAST FEEDING

If pregnant or breastfeeding:Ask a health professional before use.

Directions

Directions:Adults, or children over the age of 12: Clean and dry affected area. Remove film from patch and apply to skin (see illustration). Apply one patch at a time to affected area, not more than 3 to 4 time daily. Remove patch from the skin after at most 8-hour application. Children under 12 years of age: consult a doctor.

Keep out of reach of children and pets.If swallowed, get medical help or contact a Poison Control Center right away.

Other Information:

- Store at 68 °F-77° F (20 °C-25° C.)
- Store in a clean, dry place without direct sunlight.

Inactive Ingredients:

Dihydroxyaluminum Aminoacetate, Edetate Disodium, Glycerin, Hydroxyacetophenone, Kaolin, L(+)-Tartaric Acid, Mineral Oil, Polysorbate 80, Polyacrylic Acid, Polyvinylpyrroliodone K90, Propylene Glycol, Sodium Polyacrylate, Titanium Dioxide, Water.

Questions or Comments:833.711.8833

- info@ionpharmausa.com

PRINCIPAL DISPLAY PANEL

NDC 82944-104-10

LIDOSYNC
Lidocaine 4% Menthol 1%

TOPICAL PAIN PATCH
For Temporary Pain Relief

Flexible Patch Innovation

Soothing and Effective
Long Lasting Relief

10 FLEXIBLE PATCHES
3.94 x 5.5 (10cm x 14cm)

ION PHARMA